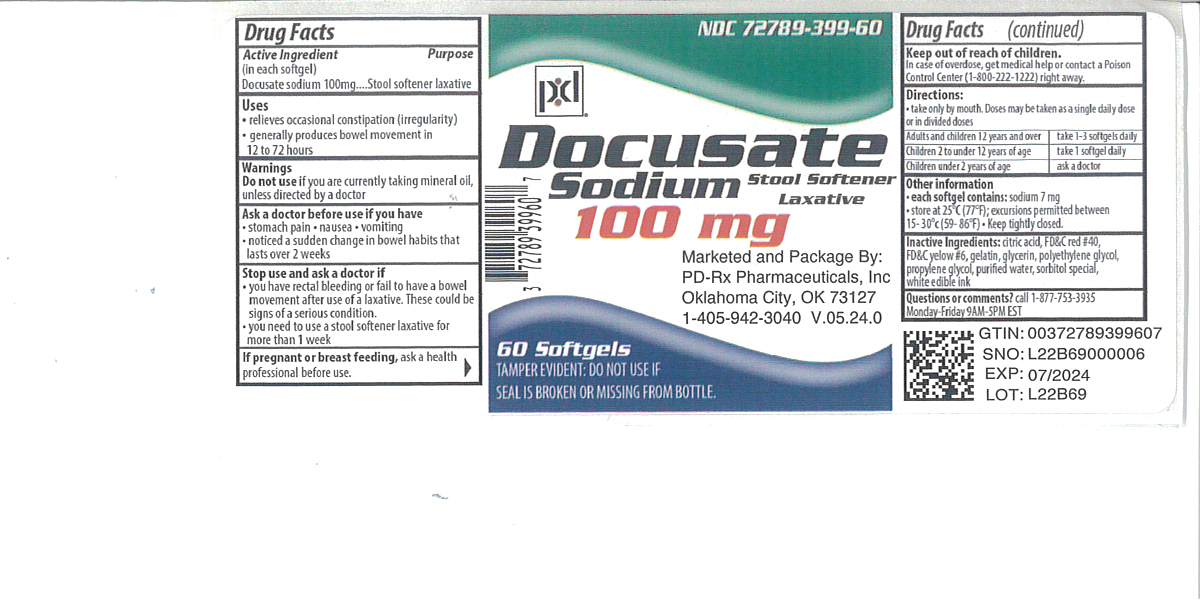 DRUG LABEL: DOCUSATE SODIUM
NDC: 72789-399 | Form: CAPSULE, LIQUID FILLED
Manufacturer: PD-Rx Pharmaceuticals, Inc.
Category: otc | Type: HUMAN OTC DRUG LABEL
Date: 20260226

ACTIVE INGREDIENTS: DOCUSATE SODIUM 100 mg/1 1
INACTIVE INGREDIENTS: FD&C RED NO. 40; FD&C YELLOW NO. 6; GELATIN; POLYETHYLENE GLYCOL, UNSPECIFIED; PROPYLENE GLYCOL; WATER; SORBITOL; GLYCERIN; CITRIC ACID MONOHYDRATE; SORBITAN

DRUG FACTS

Active ingredient (in each softgel)

Docusate sodium 100 mg

Purpose

Stool softener laxative

Uses

- relieves occasional constipation (irregularity)
- generally produces bowel movement in 12 to 72 hours

Warnings

Do not use

if you are presently taking mineral oil, unless told to do so by a doctor.

Ask a doctor before use if you have

- stomach pain
- nausea
- vomiting
- noticed a sudden change in bowel habits that lasts over 2 weeks

Stop use and ask a doctor if

- you have rectal bleeding or fail to have a bowel movement after use of a laxative. These could be signs of a serious condition.
- you need to use a stool softener laxative for more than 1 week

If pregnant or breast-feeding,

ask a health care professional before use.

Keep out of reach of children.

In case of overdose, get medical help or contact a Poison Control Center (1-800-222-1222) right away.

Directions

- take only by mouth. Doses may be taken as a single daily dose or in divided doses.

adults and children 12 years and over | take 1-3 softgels daily
children 2 to under 12 years of age | take 1 softgel daily
children under 2 years | ask a doctor

Other information

- each softgel contains:sodium 7 mg
- store at 25ºC (77ºF); excursion permitted between 15-30ºC (59-86ºF)

Inactive ingredients

citric acid, FD&C red #40, FD&C yellow #6, gelatin, glycerin, polyethylene glycol, propylene glycol, purified water, sorbitol special, white edible ink

Questions or comments?

Call 1-877-753-3935Monday-Friday 9AM-5PM EST

Principal Display Panel

docusate sodium 100 mg

stool softener laxative

TAMPER EVIDENT: DO NOT USE IF SEAL IS BROKEN OR MISSING FROM BOTTLE.